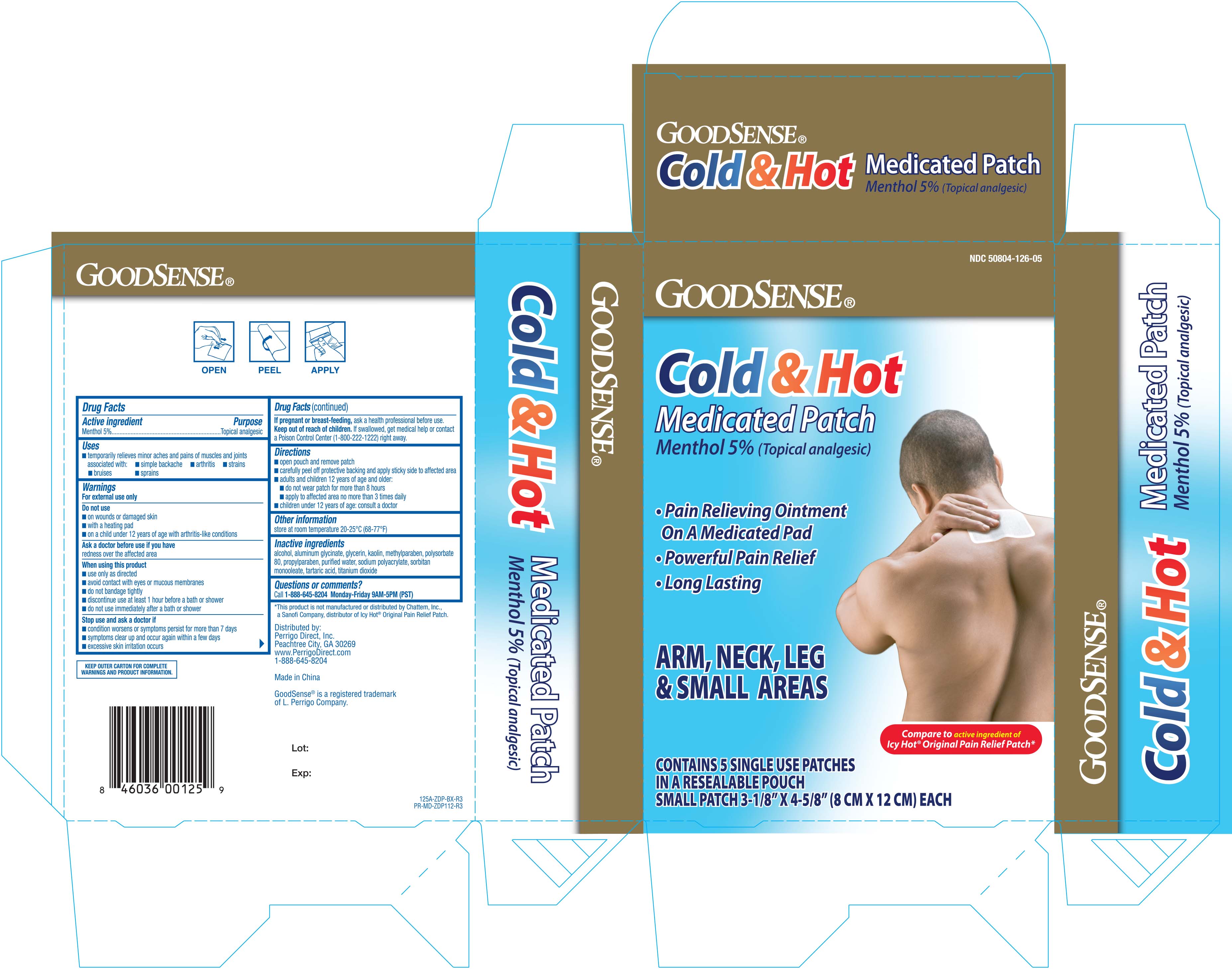 DRUG LABEL: Goodsense Extra Strength Cold and Hot Medicated
NDC: 50804-126 | Form: PATCH
Manufacturer: Geiss, Destin and Dunn, Inc.
Category: otc | Type: HUMAN OTC DRUG LABEL
Date: 20251031

ACTIVE INGREDIENTS: MENTHOL 50 mg/1 1
INACTIVE INGREDIENTS: SORBITAN MONOOLEATE; KAOLIN; ALCOHOL; GLYCERIN; DIHYDROXYALUMINUM AMINOACETATE ANHYDROUS; PROPYLPARABEN; METHYLPARABEN; TITANIUM DIOXIDE; POLYSORBATE 80; SODIUM POLYACRYLATE (2500000 MW); TARTARIC ACID; WATER

GoodSense Cold & Hot Medicated Patches 5ct Small 125A

Active ingredient Purpose

Menthol 5%.......................................................Topical analgesic

Uses

temporariliy relieves minor aches and pains of muscles and joints associated with:

- simple backache
- arthritis
- strains
- burises
- sprains

Warnings

For external use only

Do not use

- on wonunds or damaged skin
- with a heating pad
- on a child under 12 years of age with arthritis-like conditions

Ask a doctor before use if you have

- redness over the affected area

When using this product:

- use only as directed
- avoid contact with eyes or mucous membranes
- do not bandage tightly
- discontinue use at least 1 hour before a bath or shower
- do not use immediately after a bath or shower

Stop use and ask a doctor if:

- condition worsens or symptoms persist for more than 7 days
- symptoms clear up and occur again within a few days
- excessive skin irritation occurs

PREGNANCY OR BREAST FEEDING

If pregnant or breast-feeding, ask a health professional before use.

Keep out of reach of children. If swallowed, get medical help or contact a Poison Control Center (1-800-222-1222) right away.

Directions

- open pouch and remove patch
- carefully peel off protective backing and apply sticky side to affected area
- adults and children 12 years of age or older
- do not wear patch for more than 8 hours
- apply to affected area no more than 3 times daily
- children under 12 years of age: consult a doctor

Other information

- Store at room temperature 20-25°C (68-77°F)

Inactive ingredients

alcohol, aluminum glycinate, glycerin, kaolin, methylparaben, polysorbate 80, propylparaben, purified water, sodium polyacrylate, sorbitan monooleate, tartaric acid, titanium dioxide

DOSAGE AND ADMINISTRATION

Distributed By:

Perrigo Direct, Inc.

Peachtree City, Ga 30269

www.PerrigoDirect.com

1-866-696-0957

Made in China